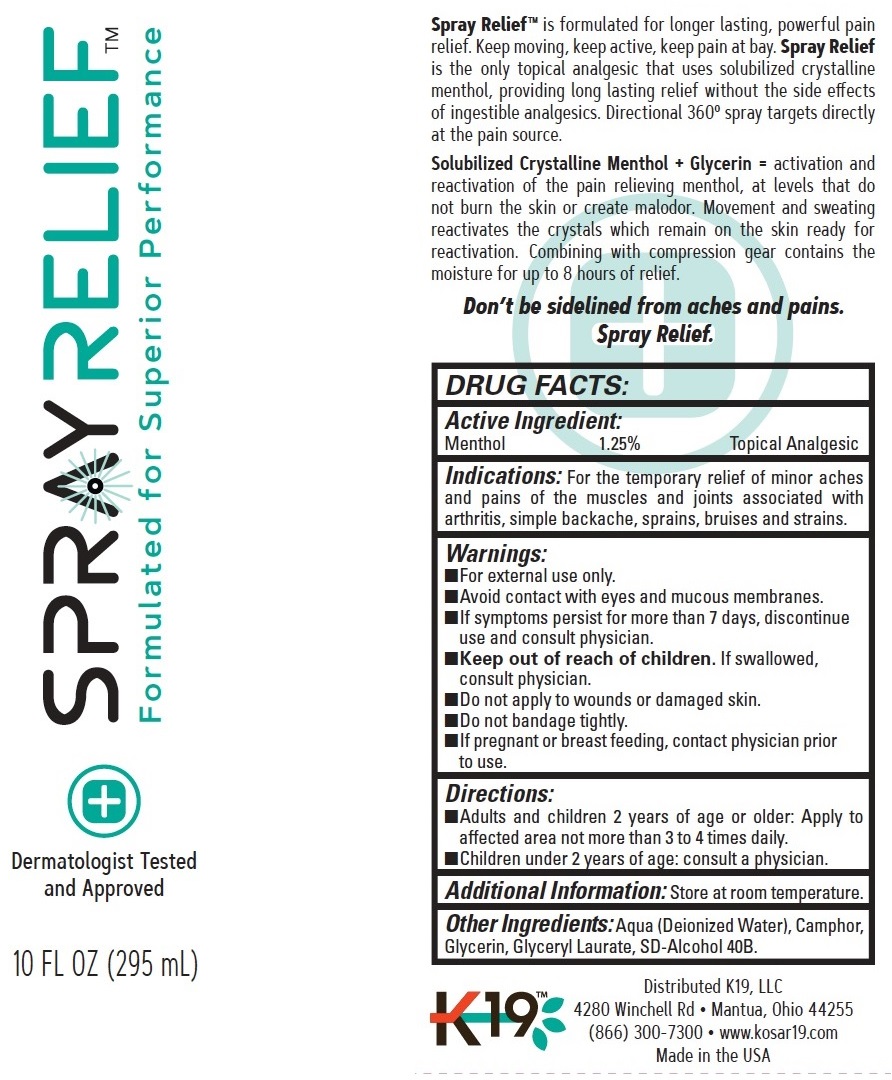 DRUG LABEL: K19 RELIEF
NDC: 83574-413 | Form: LIQUID
Manufacturer: K19 LLC
Category: otc | Type: HUMAN OTC DRUG LABEL
Date: 20250115

ACTIVE INGREDIENTS: MENTHOL 12.5 mg/1 mL
INACTIVE INGREDIENTS: WATER; CAMPHOR (SYNTHETIC); GLYCERIN; GLYCERYL LAURATE

K19 SPRAY RELIEF

Active Ingredient:

Menthol 1.25%

PURPOSE

Topical Analgesic

Indications:

For the temporary relief of minor aches and pains of the muscles and joints associated with arthritis, simple backache, sprains, bruises and stains.

Warnings:

- For external use only.
- Avoid contact with eyes and mucous membranes.
- If symptoms persist for more than 7 days, discontinue use and consult physician.

Keep Out of reach of children.

- If swallowed, consult physician.
- Do not apply to wounds or damaged skin.
- Do not bandage tightly.

If pregnant or breast feeding,

contact physician prior to use.

Directions:

- Adults and children 2 years of age or older: Apply to affected area not more than 3 to 4 times daily.
- Chidlren under 2 years of age: consult a physician.

Additional Information:

Store at room temperature.

Other Ingredients:

Aqua (Deionized Water), Camphor, Glycerin, Glyceryl Laurate, SD-Alcohol 40B.